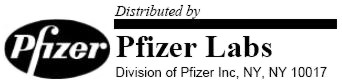 DRUG LABEL: Unknown
Manufacturer: Pfizer Labs
Category: prescription | Type: HUMAN PRESCRIPTION DRUG LABELING
Date: 20051214

RENESE®
(polythiazide)
TABLETS
for Oral Administration

DESCRIPTION

Renese® is designated generically as polythiazide, and chemically as 2H-1,2,4-Benzothiadiazine-7-sulfonamide, 6-chloro-3,4-dihydro-2-methyl-3-[[(2,2,2-trifluoroethyl)thio]methyl]-, 1,1-dioxide. It is a white crystalline substance, insoluble in water but readily soluble in alkaline solution.

Inert Ingredients: dibasic calcium phosphate; lactose; magnesium stearate; polyethylene glycol; sodium lauryl sulfate; starch; vanillin. The 2 mg tablets also contain: Yellow 6; Yellow 10.

ACTION

The mechanism of action results in an interference with the renal tubular mechanism of electrolyte reabsorption. At maximal therapeutic dosage all thiazides are approximately equal in their diuretic potency. The mechanism whereby thiazides function in the control of hypertension is unknown.

INDICATIONS

Renese is indicated as adjunctive therapy in edema associated with congestive heart failure, hepatic cirrhosis, and corticosteroid and estrogen therapy.

Renese has also been found useful in edema due to various forms of renal dysfunction as: Nephrotic syndrome; Acute glomerulonephritis; and Chronic renal failure.

Renese is indicated in the management of hypertension either as the sole therapeutic agent or to enhance the effectiveness of other antihypertensive drugs in the more severe forms of hypertension.

Usage in Pregnancy

The routine use of diuretics in an otherwise healthy woman is inappropriate and exposes mother and fetus to unnecessary hazard. Diuretics do not prevent development of toxemia of pregnancy, and there is no satisfactory evidence that they are useful in the treatment of developed toxemia.

Edema during pregnancy may arise from pathological causes or from the physiologic and mechanical consequences of pregnancy. Thiazides are indicated in pregnancy when edema is due to pathologic causes, just as they are in the absence of pregnancy (however, see Warnings, below). Dependent edema in pregnancy, resulting from restriction of venous return by the expanded uterus, is properly treated through elevation of the lower extremities and use of support hose; use of diuretics to lower intravascular volume in this case is illogical and unnecessary. There is hypervolemia during normal pregnancy which is harmful to neither the fetus nor the mother (in the absence of cardiovascular disease), but which is associated with edema, including generalized edema, in the majority of pregnant women. If this edema produces discomfort, increased recumbency will often provide relief. In rare instances, this edema may cause extreme discomfort which is not relieved by rest. In these cases, a short course of diuretics may provide relief and may be appropriate.

CONTRAINDICATIONS

Anuria. Hypersensitivity to this or other sulfonamide derived drugs.

WARNINGS

Thiazides should be used with caution in severe renal disease. In patients with renal disease, thiazides may precipitate azotemia. Cumulative effects of the drug may develop in patients with impaired renal function.

Thiazides should be used with caution in patients with impaired hepatic function or progressive liver disease, since minor alterations of fluid and electrolyte balance may precipitate hepatic coma.

Thiazides may add to or potentiate the action of other antihypertensive drugs. Potentiation occurs with ganglionic or peripheral adrenergic blocking drugs.

Sensitivity reactions may occur in patients with a history of allergy or bronchial asthma.

The possibility of exacerbation or activation of systemic lupus erythematosus has been reported.

Usage in Pregnancy

Thiazides cross the placental barrier and appear in cord blood. The use of thiazides in pregnant women requires that the anticipated benefit be weighed against possible hazards to the fetus. These hazards include fetal or neonatal jaundice, thrombocytopenia, and possibly other adverse reactions which have occurred in the adult.

Nursing Mothers

Thiazides appear in breast milk. If use of the drug is deemed essential, the patient should stop nursing.

PRECAUTIONS

Periodic determination of serum electrolytes to detect possible electrolyte imbalance should be performed at appropriate intervals.

All patients receiving thiazide therapy should be observed for clinical signs of fluid or electrolyte imbalance; namely, hyponatremia, hypochloremic alkalosis, and hypokalemia. Serum and urine electrolyte determinations are particularly important when the patient is vomiting excessively or receiving parenteral fluids. Medication such as digitalis may also influence serum electrolytes. Warning signs, irrespective of cause, are: dryness of mouth, thirst, weakness, lethargy, drowsiness, restlessness, muscle pains or cramps, muscular fatigue, hypotension, oliguria, tachycardia, and gastrointestinal disturbances such as nausea and vomiting.

Hypokalemia may develop with thiazides as with any other potent diuretic, especially with brisk diuresis, when severe cirrhosis is present, or during concomitant use of corticosteroids or ACTH.

Interference with adequate oral electrolyte intake will also contribute to hypokalemia. Digitalis therapy may exaggerate metabolic effects of hypokalemia especially with reference to myocardial activity.

Any chloride deficit is generally mild and usually does not require specific treatment except under extraordinary circumstances (as in liver disease or renal disease). Dilutional hyponatremia may occur in edematous patients in hot weather; appropriate therapy is water restriction, rather than administration of salt except in rare instances when the hyponatremia is life threatening. In actual salt depletion, appropriate replacement is the therapy of choice.

Hyperuricemia may occur or frank gout may be precipitated in certain patients receiving thiazide therapy.

Insulin requirements in diabetic patients may be increased, decreased, or unchanged. Latent diabetes mellitus may become manifest during thiazide administration.

Thiazide drugs may increase the responsiveness to tubocurarine.

The antihypertensive effects of the drug may be enhanced in the postsympathectomy patient.

Thiazides may decrease arterial responsiveness to norepinephrine. This diminution is not sufficient to preclude effectiveness of the pressor agent for therapeutic use.

If progressive renal impairment becomes evident, as indicated by a rising nonprotein nitrogen or blood urea nitrogen, a careful reappraisal of therapy is necessary with consideration given to withholding or discontinuing diuretic therapy.

Thiazides may decrease serum PBI levels without signs of thyroid disturbance.

Pediatric Use

Safety and effectiveness in pediatric patients have not been established.

ADVERSE REACTIONS

A. GASTROINTESTINAL SYSTEM REACTIONS

1. anorexia
2. gastric irritation
3. nausea
4. vomiting
5. cramping
6. diarrhea
7. constipation
8. jaundice (intrahepatic cholestatic jaundice)
9. pancreatitis

B. CENTRAL NERVOUS SYSTEM REACTIONS

1. dizziness
2. vertigo
3. paresthesias
4. headache
5. xanthopsia

C. HEMATOLOGIC REACTIONS

1. leukopenia
2. agranulocytosis
3. thrombocytopenia
4. aplastic anemia

D. DERMATOLOGIC—HYPERSENSITIVITY REACTIONS

1. purpura
2. photosensitivity
3. rash
4. urticaria
5. necrotizing angiitis
  (vasculitis)
  (cutaneous vasculitis)

E. CARDIOVASCULAR REACTION

Orthostatic hypotension may occur and may be aggravated by alcohol, barbiturates or narcotics.

F. OTHER

1. hyperglycemia
2. glycosuria
3. hyperuricemia
4. muscle spasm
5. weakness
6. restlessness

Whenever adverse reactions are moderate or severe, thiazide dosage should be reduced or therapy withdrawn.

DOSAGE AND ADMINISTRATION

Therapy should be individualized according to patient response. This therapy should be titrated to gain maximal therapeutic response as well as the minimal dose possible to maintain that therapeutic response. The usual dosage of Renese tablets for diuretic therapy is 1 to 4 mg daily, and for antihypertensive therapy is 2 to 4 mg daily.

HOW SUPPLIED

RENESE (polythiazide) Tablets are available as:

1 mg white, scored tablets in bottles of 100 (NDC 0069-3750-66).

2 mg yellow, scored tablets in bottles of 100 (NDC 0069-3760-66).

4 mg white, scored tablets in bottles of 100 (NDC 0069-3770-66).

Rx Only

69-1116-00-6

April 1997